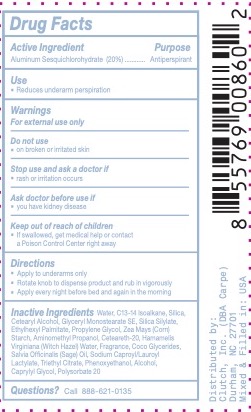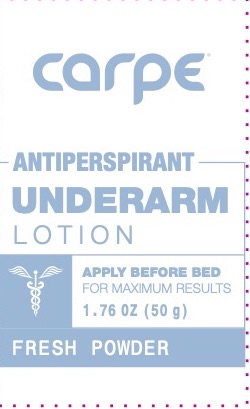 DRUG LABEL: Carpe Antiperspirant Fresh Powder
NDC: 74307-829 | Form: STICK
Manufacturer: Clutch Inc
Category: otc | Type: HUMAN OTC DRUG LABEL
Date: 20260226

ACTIVE INGREDIENTS: ALUMINUM SESQUICHLOROHYDRATE 20 g/100 g
INACTIVE INGREDIENTS: POLYSORBATE 20; ETHYLHEXYL PALMITATE; SODIUM CAPROYL LACTYLATE; PHENOXYETHANOL; ALCOHOL; SILICA; CETEARETH-20; SAGE OIL; AMINOMETHYL PROPANOL; TRIETHYL CITRATE; GLYCERYL STEARATE SE; HAMAMELIS VIRGINIANA TOP WATER; COCOGLYCERIDES; ZEA MAYS (CORN) STARCH; WATER; C13-14 ISOPARAFFIN; CETEARYL ALCOHOL; PROPYLENE GLYCOL; CAPRYLYL GLYCOL

CARPE ANTIPERSPIRANT FRESH POWDER

ACTIVE INGREDIENT

Aluminum Sesquichlorohydrate 20%

PURPOSE

Anti-perspirant

INDICATIONS AND USAGE

Reduces underarm perspiration.

WARNINGS

For external use only.

Do not useon broken or irritated skin

Stop use and ask a doctor ifrash or irritation occurs

Ask a doctor before use ifyou have kidney disease

KEEP OUT OF REACH OF CHILDREN

If swallowed, get medical help or contact a Poison Control Center right away.

DOSAGE AND ADMINISTRATION

Apply to underarms only

Rotate knob to dispense product and rub in vigorously

Apply every night before going to bed and again in the morning

INACTIVE INGREDIENT

Water, C13-14 Isoalkane, Silica, Cetearyl Alcohol, Glyceryl Monostearate SE, Silica Silylate, Ethyhexyl Palmitate, Propylene Glycol, Zea Mays (Corn) Starch, Aminomethyl Propanol, Ceteareth-20, Hamamelis Virginiana (Witch Hazel) Water, Fragrance, Coco Glycerides, Salvia Officinalis (Sage) Oil, Sodium Caproyl/Lauroyl Lactylate, Triethyl Citrate, Phenoxyethanol, Alcohol, Caprylyl Glycol, Polysorbate 20